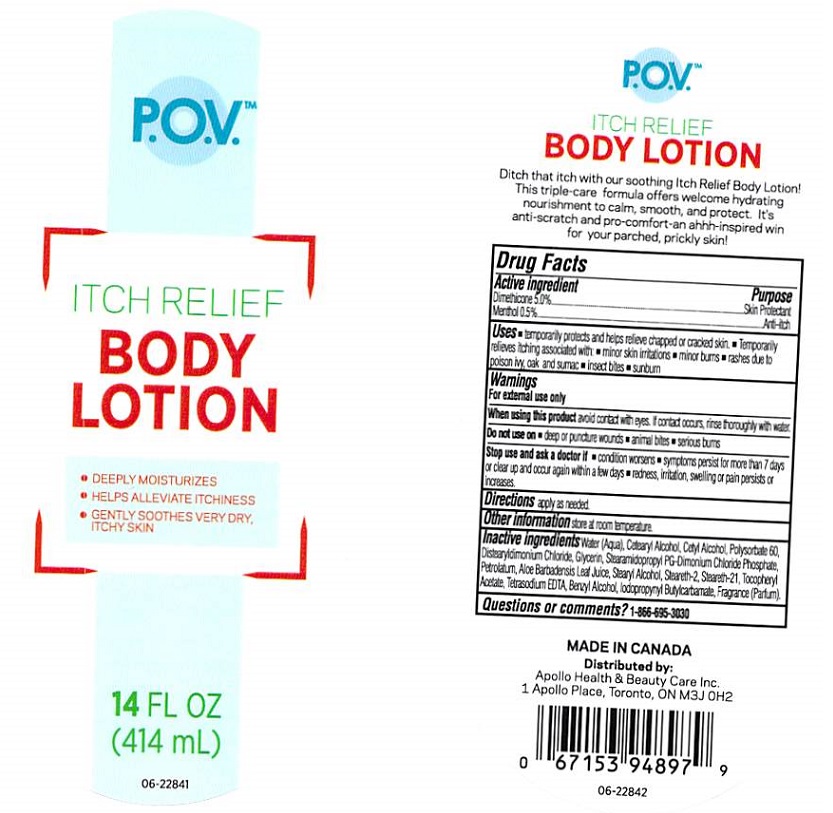 DRUG LABEL: P.O.V Itch Relief Body
NDC: 63148-562 | Form: LOTION
Manufacturer: Apollo Health and Beauty Care Inc.
Category: otc | Type: HUMAN OTC DRUG LABEL
Date: 20180329

ACTIVE INGREDIENTS: DIMETHICONE 50 mg/1 mL; MENTHOL 5 mg/1 mL
INACTIVE INGREDIENTS: WATER; CETOSTEARYL ALCOHOL; CETYL ALCOHOL; POLYSORBATE 60; DISTEARYLDIMONIUM CHLORIDE; GLYCERIN; STEARAMIDOPROPYL PG-DIMONIUM CHLORIDE PHOSPHATE; PETROLATUM; ALOE VERA LEAF; STEARYL ALCOHOL; STEARETH-2; STEARETH-21; .ALPHA.-TOCOPHEROL ACETATE, DL-; EDETATE SODIUM; BENZYL ALCOHOL; IODOPROPYNYL BUTYLCARBAMATE

Drug Facts

Active ingredients

Dimethicone 5.0%, Menthol 0.5%

Purpose

Skin Protectant, Anti-itch

Uses

- temporarily protects and helps relieve chapped or cracked skin.
- temporarily relieves itching associated with: minor skin irritations, minor burns, rashes due to poison ivy, oak and sumac
- insect bites
- sunburn

Warnings

For external use only

When using this product

avoid contact with eyes. If contact occurs, rinse thoroughly with water.

Do not use on

- deep or puncture wournds
- animal bites
- serious burns

Stop use and ask a doctor if

- condition worsens
- symptoms persist for more than 7 days or clear up and occur again within a few days
- redness, irritation, swelling or pain persists or increases

Keep out of reach of children.

In case of accidental ingestion, get medical help or contact a Poison Control Center immediately.

Directions

apply as needed

Other information

store at room temperature.

Inactive ingredients

Water (Aqua), Cetearyl Alcohol, Cetyl Alcohol, Polysorbate 60, Distearyldimonium Chloride, Glycerin, Stearamidopropyl PG-Dimonium Chloride Phosphate, Petrolatum, Aloe Barbadensis Leaf Juice, Stearyl Alcohol, Steareth-2, Steareth-21, Tocopheryl Acetate, Tetrasodium EDTA, Benzyl Alcohol, Iodopropynyl Butylcarbamate, Fragrance (Parfum).

Questions or comments?

1-866-695-3030